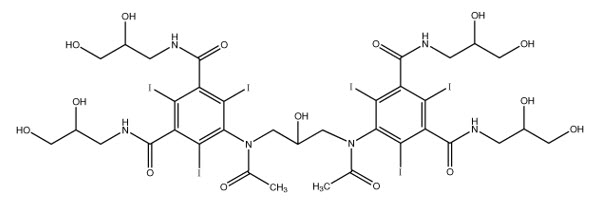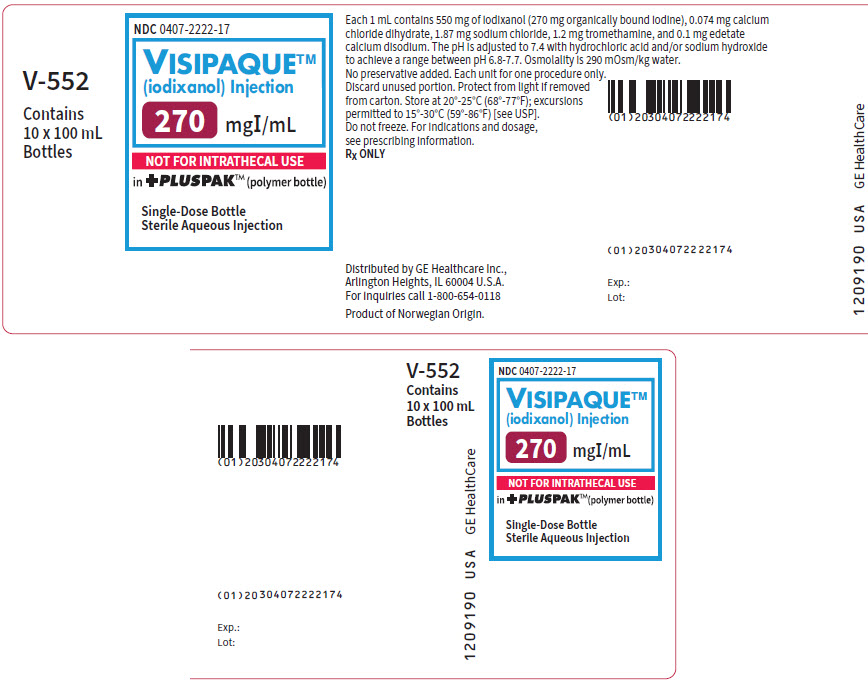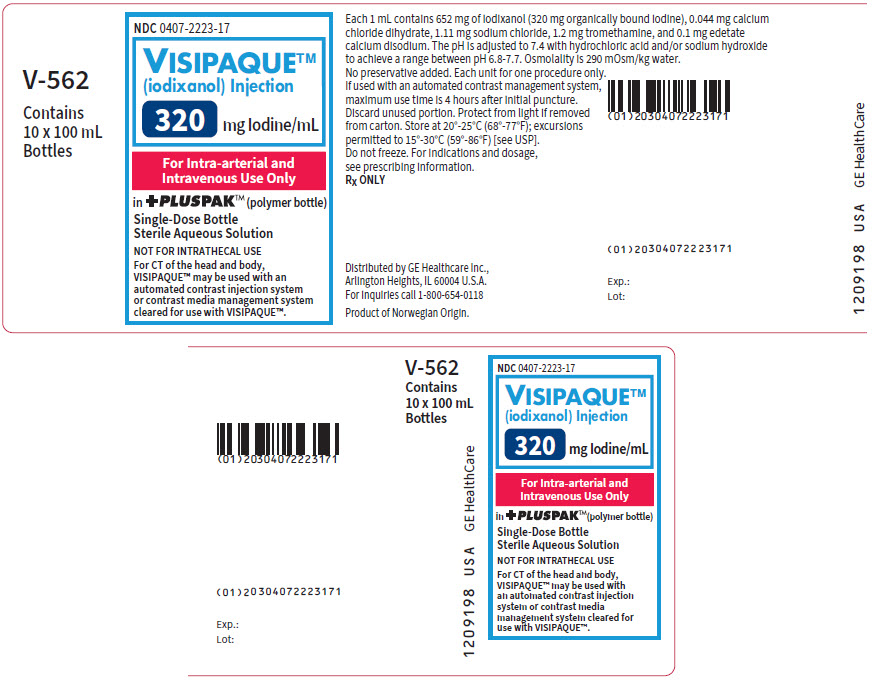 DRUG LABEL: Visipaque
NDC: 0407-2222 | Form: INJECTION, SOLUTION
Manufacturer: GE Healthcare Inc.
Category: prescription | Type: HUMAN PRESCRIPTION DRUG LABEL
Date: 20251010

ACTIVE INGREDIENTS: Iodixanol 270 mg/1 mL
INACTIVE INGREDIENTS: calcium chloride 0.074 mg/1 mL; sodium chloride 1.87 mg/1 mL; tromethamine 1.2 mg/1 mL; edetate calcium disodium 0.1 mg/1 mL; hydrochloric acid; sodium hydroxide

HIGHLIGHTS OF PRESCRIBING INFORMATION

These highlights do not include all the information needed to use VISIPAQUE safely and effectively. See full prescribing information for VISIPAQUE.
VISIPAQUE (iodixanol) injection, for intra-arterial or intra-venous use
Initial U.S. Approval: 1996

WARNING: NOT FOR INTRATHECAL USE

See full prescribing information for complete boxed warning

Inadvertent intrathecal administration may cause death, convulsions/seizures, cerebral hemorrhage, coma, paralysis, arachnoiditis, acute renal failure, cardiac arrest, rhabdomyolysis, hyperthermia, and brain edema. (4, 5.1)

1 INDICATIONS AND USAGE

VISIPAQUE injection is a radiographic contrast agent indicated for the following:

Intra-arterial Procedures (1.1)

Adults and pediatric patients 12 years of age and over

- Intra-arterial digital subtraction angiography (270 and 320 mg Iodine/mL).
- Angiocardiography (left ventriculography and selective coronary arteriography), peripheral arteriography, visceral arteriography, and cerebral arteriography (320 mg Iodine/mL).

Pediatric patients less than 12 years of age

- Angiocardiography, cerebral arteriography, and visceral arteriography (320 mg Iodine/mL).

Intravenous Procedures (1.2)

Adults and pediatric patients 12 years of age and over

- Computed tomography (CT) imaging head and body (270 and 320 mg Iodine/mL).
- Excretory urography (270 and 320 mg Iodine/mL).
- Peripheral venography (270 mg Iodine/mL).
- Coronary computed tomography angiography (CCTA) to assist diagnostic evaluation of patients with suspected coronary artery disease (320 mg Iodine/mL).

Pediatric patients less than 12 years of age

- CT imaging of the head and body (270 mg Iodine/mL).
- Excretory urography (270 mg Iodine/mL).

2 DOSAGE AND ADMINISTRATION

- Individualize the combination of volume and concentration of VISIPAQUE Injection considering age, body weight, size of the vessel, rate of blood flow within the vessel, and other applicable factors. (2.1, 2.2, 2.3, 2.4)
- For CT of the head and body, VISIPAQUE may be used with an automated contrast injection system or contrast media management system cleared for use with VISIPAQUE. (2.5)
- For the adult patients, the maximum recommended total dose of iodine is 80 grams. (2.1)
- Patients should be adequately hydrated prior to and following the intravascular administration of iodinated contrast agents. (2.1, 5.3)
- See full prescribing information for complete dosing and administration information. (2)

3 DOSAGE FORMS AND STRENGTHS

Injection: In concentrations of 270 and 320 mg of organically bound iodine per mL (550 mg and 652 mg of Iodixanol per mL). (3)

4 CONTRAINDICATIONS

- Not indicated for intrathecal use. (4)

5 WARNINGS AND PRECAUTIONS

- Hypersensitivity Reactions: Life-threatening or fatal reactions can occur. Always have emergency equipment and trained personnel available. (5.2)
- Contrast-Induced Acute Kidney Injury: Acute injury including renal failure can occur. Minimize dose and maintain adequate hydration to minimize risk. (5.3)
- Cardiovascular adverse reactions: Hemodynamic disturbances including shock and cardiac arrest may occur during or after administration. (5.4)
- Thyroid dysfunction in pediatric patients 0 to 3 Years of Age: Individualize thyroid function monitoring based on risk factors such as prematurity. (5.8)

6 ADVERSE REACTIONS

Most common adverse reactions (incidence greater than 0.5%) in adult patients after VISIPAQUE injection: Discomfort, warmth, pain; Cardiovascular: angina. Gastrointestinal: diarrhea, nausea, vomiting. Nervous System: agitation, anxiety, insomnia, nervousness, dizziness, headache, migraine, unusual skin sensations, sensory disturbance, fainting, sensation of spinning. Skin: itchy rash, severe itching, hives. Special Senses: Smell, taste, and vision alteration. (6.1) Pediatric patients experienced similar adverse reactions. (6.3)

To report SUSPECTED ADVERSE REACTIONS, contact GE HealthCare at 1-800-654-0118 or FDA at 1-800-FDA-1088 or www.fda.gov/medwatch.

8 USE IN SPECIFIC POPULATIONS

- Lactation: A lactating woman may pump and discard breast milk for 10 hours after VISIPAQUE administration. (8.2)
- Geriatrics: Exercise caution in dose selection for elderly patients. (8.5)

FULL PRESCRIBING INFORMATION

WARNING: NOT FOR INTRATHECAL USE

Inadvertent intrathecal administration may cause death, convulsions/seizures, cerebral hemorrhage, coma, paralysis, arachnoiditis, acute renal failure, cardiac arrest, rhabdomyolysis, hyperthermia, and brain edema [see Contraindications (4) and Adverse Reactions (5.1)].

1 INDICATIONS AND USAGE

VISIPAQUE is indicated for:

1.1 Intra-arterial Procedures

Adult and pediatric patients 12 years of age and older

- (270 and 320 mg Iodine/mL) intra-arterial digital subtraction angiography (IA-DSA).
- (320 mg Iodine/mL) angiocardiography (left ventriculography and selective coronary arteriography), peripheral arteriography, visceral arteriography, and cerebral arteriography.

Pediatric patients less than 12 years of age

- (320 mg Iodine/mL) angiocardiography, cerebral arteriography, and visceral arteriography.

1.2 Intravenous Procedures

Adult and pediatric patients 12 years of age and older

- (270 and 320 mg Iodine/mL) CT imaging of the head and body.
- (270 and 320 mg Iodine/mL) excretory urography.
- (270 mg Iodine/mL) peripheral venography.
- (320 mg Iodine/mL) coronary computed tomography angiography (CCTA) to assist in the diagnostic evaluation of patients with suspected coronary artery disease.

Pediatric patients less than 12 years of age

- (270 mg Iodine/mL) CT imaging of the head and body.
- (270 mg Iodine/mL) excretory urography.

2 DOSAGE AND ADMINISTRATION

2.1 Important Dosage and Administration Instructions

- VISIPAQUE is for intravascular use only [see Boxed Warning, Contraindications (4), and Warnings and Precautions (5.1)]
- Use sterile technique for all handling and administration of VISIPAQUE.
- Do not use if tamper-evident ring is broken or missing.
- Warm VISIPAQUE and administer at body or room temperature.
- Inspect VISIPAQUE for particulate matter or discoloration before administration, whenever solution and container permit. Do not administer if VISIPAQUE contains particulate matter or is discolored.
- Do not mix VISIPAQUE with, or inject in intravenous lines containing, other drugs or total nutritional admixtures.
- Use the lowest dose necessary to obtain adequate visualization.
- Individualize the volume, strength, and rate of administration of VISIPAQUE. Consider factors such as age, bodyweight, vessel size, blood flow rate within the vessel, anticipated pathology, degree and extent of opacification required, structures or area to be examined, disease processes affecting the patient, and equipment and technique to be employed.
- The maximum recommended total dose of iodine for adults is 80 grams.
- Avoid extravasation when injecting VISIPAQUE; especially in patients with severe arterial or venous disease [see Warnings and Precautions (5.6)].
- Hydrate patients before and after VISIPAQUE administration [see Warnings and Precautions (5.3)].

2.2 Intra-Arterial Dosage and Administration

- Intra-arterial digital subtraction angiography (IA-DSA) (270 and 320 mg Iodine/mL)
- Angiocardiography (left ventriculography and selective coronary arteriography), peripheral arteriography, visceral arteriography, and cerebral arteriography (320 mg Iodine/mL)

Use Injection rates approximately equal to the flow rate in the vessel being injected. The usual single injection volumes or total dose per patient (mL/kg) for adults and adolescents over 12 years of age are listed in Table 1.

TABLE 1 ADULTS and PEDIATRIC PATIENTS 12 YEARS OF AGE AND OLDER VISIPAQUE SINGLE DOSE RECOMMENDATIONS FOR INJECTION INTO SELECTED ARTERIES
 | ARTERIOGRAPHY | IA-DSA [IA-DSA = Intra-Arterial Digital Subtraction Angiography] |  | Maximum Total Dose
Intra-Arterial Injection Sites | 320 mg Iodine/mL | 270 mg Iodine/mL | 320 mg Iodine/mL | Maximum Total Dose
Carotid Arteries | 10 to 14 mL |  | 5 to 8 mL | Usually Not to Exceed 175 mL
Vertebral Arteries | 10 to 12 mL |  | 5 to 8 mL | Usually Not to Exceed 175 mL
Right Coronary Artery | 3 to 8 mL |  |  | Usually Not to Exceed 200 mL
Left Coronary Artery | 3 to 10 mL |  |  | Usually Not to Exceed 200 mL
Left Ventricle | 20 to 45 mL
Renal Arteries | 8 to 18 mL | 10 to 25 mL | -- | Usually Not to Exceed 250 mL
Aortography | 30 to 70 mL | 20 to 50 mL | 10 to 50 mL | Usually Not to Exceed 250 mL
Major Branches of Aorta | 10 to 70 mL | 5 to 30 mL | 2 to 10 mL
Aortofemoral Runoffs | 20 to 90 mL | -- | 6 to 15 mL
Peripheral Arteries | 15 to 30 mL | -- | 3 to 15 mL

2.3 Intravenous Dosage and Administration

- Computed Tomography of the Head or Body (270 mg Iodine/mL and 320 mg Iodine/mL)
- Excretory Urography (270 mg Iodine/mL and 320 mg Iodine/mL)
- Peripheral Venography (270 mg Iodine/mL)
- Coronary Computed Tomography Angiography (CCTA) (320 mg Iodine/mL)

Recommended dosage of VISIPAQUE is dependent on: the administration procedure, patient weight, and CT device factors, as detailed in Table 2. Calibrate the intravenous injection rate so that image acquisition coincides with peak arterial concentration. The time between VISIPAQUE injection and peak arterial concentration varies between patients. Selected dosing for different indications in adults and pediatric patients over 12 years of age are shown in Table 2.

TABLE 2 ADULTS and PEDIATRIC PATIENTS 12 YEARS OF AGE AND OLDER VISIPAQUE DOSING RECOMMENDATIONS FOR INTRAVENOUS CONTRAST ADMINISTRATION
Study Type | Comment | 270 mg Iodine/mL | 320 mg Iodine/mL | Maximum Total Volume
CT of Head or Body [For CT of the head and body, VISIPAQUE may be used with an automated contrast injection system or contrast media management system cleared for use with VISIPAQUE.] | Bolus Infusion | 75 to 150 mL 100 to 150 mL | 75 to 150 mL 100 to 150 mL | 150 mL
Excretory Urography | Normal Renal Function | 1 mL/kg | 1 mL/kg | 100 mL
Venography | Per lower extremity | 50 to 150 mL |  | 250 mL
CCTA, [For pediatric patients aged 12 to 17, recommended dose is 1 to 2 mL/kg.] | Bolus injection with test bolus [The main VISIPAQUE volume may be preceded by a test bolus consisting of 20 mL VISIPAQUE, immediately followed by a 20 mL saline flush, both injected at rate of 4 to 7 mL/sec.] or bolus tracking |  | 50 to 150 mL [Injection of VISIPAQUE with saline can be either biphasic (without dilution phase) or triphasic (with dilution phase). Alternatively, a dose of 1 mL/kg may be used to calculate total VISIPAQUE dose (excluding any test bolus). For CCTA acquired at < 120 kVp, the dose of VISIPAQUE may be reduced by up to 15% in patients < 85 kg and BMI < 30 kg/m^2. For CCTA acquired on a scanner with more than 64 detector rows, the dose of VISIPAQUE may be reduced in proportion to the scan duration.] (4 to 7 mL per second) | 150 mL

2.4 Dosage in Pediatric Patients Less Than 12 Years of Age

Intra-arterial Dosage and Administration

Angiocardiography, cerebral arteriography, or visceral arteriography (320 mg Iodine/mL):

The recommended dosage is 1 to 2 mL/kg. The maximum dose should not exceed 4 mL/kg.

Intravenous Dosage and Administration

Computerized Tomography or Excretory Urography (270 mg Iodine/mL):

The recommended dosage is 1 to 2 mL/kg. The maximum dose should not exceed 2 mL/kg.

2.5 Instructions for Use with an Automated Contrast Injection System or Contrast Management System for CT of the Head and Body

- VISIPAQUE may be used with an automated contrast injection system cleared for use with contrast media.
  - See above Important Dosage and Administration Instructions for VISIPAQUE (2.1).
  - See device labeling for information on device indications, instructions for use, and techniques to help assure safe use.
- VISIPAQUE 320 mg Iodine/mL in 100 mL and 150 mL bottles may be used with a contrast media management system cleared for use with VISIPAQUE 320 in 100 mL and 150 mL bottles.
  - See device labeling for information on device indications, instructions for use, and techniques to help assure safe use.
  - Use sterile technique for penetrating the container closure of VISIPAQUE 320 and transferring VISIPAQUE solution. Clean the stopper with a pad soaked in sporicidal solution followed by a pad soaked in alcohol, then puncture the stopper. The container closure may be penetrated only one time with a suitable sterile component of the contrast media management system cleared for use with VISIPAQUE 320 in 100 mL and 150 mL bottles.
  - Once the VISIPAQUE 320 Injection is punctured do not remove the bottle from the work area during the entire period of use.
  - Maximum use time is 4 hours after initial puncture.
  - Each bottle is for one procedure only. Discard unused portion.

3 DOSAGE FORMS AND STRENGTHS

Injection: Non-ionic, isotonic, water-soluble, sterile, pyrogen-free, colorless to pale yellow solution in the following strengths:

- 270 mg of organically bound iodine per mL (550 mg Iodixanol per mL)
- 320 mg of organically bound iodine per mL (652 mg Iodixanol per mL)

Available in the following format: Single-dose polymer bottle (+PLUSPAK™)

4 CONTRAINDICATIONS

VISIPAQUE is contraindicated for intrathecal use [see Warnings and Precautions (5.1)].

5 WARNINGS AND PRECAUTIONS

5.1 Risks Associated with Inadvertent Intrathecal Administration

VISIPAQUE is for intravascular use only and is contraindicated for intrathecal use [see Contraindications (4) and Dosage and Administration (2.1)]. Inadvertent Intrathecal administration can cause death, convulsions/seizures, cerebral hemorrhage, coma, paralysis, arachnoiditis, acute renal failure, cardiac arrest, rhabdomyolysis, hyperthermia, and brain edema.

5.2 Hypersensitivity Reactions

VISIPAQUE can cause life-threatening or fatal hypersensitivity reactions including anaphylaxis. Manifestations include respiratory arrest, laryngospasm, bronchospasm, angioedema, and shock. Most severe reactions develop shortly after the start of the injection (within 3 minutes), but reactions can occur up to hours later. There is an increased risk in patients with a history of a previous reaction to contrast agent, and known allergies (i.e., bronchial asthma, drug, or food allergies) or other hypersensitivities. Premedication with antihistamines or corticosteroids does not prevent serious life-threatening reactions, but may reduce both their incidence and severity.

Obtain a history of allergy, hypersensitivity, or hypersensitivity reactions to iodinated contrast agents and always have emergency resuscitation equipment and trained personnel available prior to VISIPAQUE administration. Monitor all patients for hypersensitivity reactions.

5.3 Contrast-Induced Acute Kidney Injury

Acute kidney injury, including renal failure, may occur after VISIPAQUE administration. Risk factors include: pre-existing renal impairment, dehydration, diabetes mellitus, congestive heart failure, advanced vascular disease, elderly age, concomitant use of nephrotoxic or diuretic medications, multiple myeloma / paraproteinaceous diseases, repetitive and/or large doses of an iodinated contrast agent.

Use the lowest necessary dose of VISIPAQUE in patients with renal impairment. Adequately hydrate patients prior to and following VISIPAQUE administration. Do not use laxatives, diuretics, or preparatory dehydration prior to VISIPAQUE administration.

5.4 Cardiovascular Adverse Reactions

Life-threatening or fatal cardiovascular reactions including hypotension, shock, cardiac arrest have occurred with the use of VISIPAQUE. Most deaths occur during injection or five to ten minutes later, with cardiovascular disease as the main aggravating factor. Cardiac decompensation, serious arrhythmias, and myocardial ischemia or infarction can occur during coronary arteriography and ventriculography.

Based upon clinical literature reported deaths from the administration of iodinated contrast agents range from 6.6 per million (0.00066%) to 1 in 10,000 (0.01%). Use the lowest necessary dose of VISIPAQUE in patients with congestive heart failure and always have emergency resuscitation equipment and trained personnel available. Monitor all patients for severe cardiovascular reactions.

5.5 Thromboembolic Events

Angiocardiography

Serious, rarely fatal, thromboembolic events causing myocardial infarction and stroke can occur during angiocardiography procedures with both ionic and nonionic contrast media. During these procedures, increased thrombosis and activation of the complement system occurs. Risk factors for thromboembolic events include: length of procedure, catheter and syringe material, underlying disease state, and concomitant medications.

To minimize thromboembolic events, use meticulous angiographic techniques, and minimize the length of the procedure. Avoid blood remaining in contact with syringes containing iodinated contrast agents, which increases the risk of clotting. Avoid angiocardiography in patients with homocystinuria because of the risk of inducing thrombosis and embolism.

5.6 Extravasation and Injection Site Reactions

Extravasation of VISIPAQUE Injection may cause tissue necrosis and/or compartment syndrome, particularly in patients with severe arterial or venous disease. Ensure intravascular placement of catheters prior to injection. Monitor patients for extravasation and advise patients to seek medical care for progression of symptoms.

5.7 Thyroid Storm in Patients with Hyperthyroidism

Thyroid storm has occurred after the intravascular use of iodinated contrast agents in patients with hyperthyroidism, or with an autonomously functioning thyroid nodule. Evaluate the risk in such patients before use of VISIPAQUE.

5.8 Thyroid Dysfunction in Pediatric Patients 0 to 3 Years of Age

Thyroid dysfunction characterized by hypothyroidism or transient thyroid suppression has been reported after both single exposure and multiple exposures to iodinated contrast media (ICM) in pediatric patients 0 to 3 years of age.

Younger age, very low birth weight, prematurity, underlying medical conditions affecting thyroid function, admission to neonatal or pediatric intensive care units, and congenital cardiac conditions are associated with an increased risk of hypothyroidism after ICM exposure. Pediatric patients with congenital cardiac conditions may be at the greatest risk given that they often require high doses of contrast during invasive cardiac procedures.

An underactive thyroid during early life may be harmful for cognitive and neurological development and may require thyroid hormone replacement therapy. After exposure to ICM, individualize thyroid function monitoring based on underlying risk factors, especially in term and preterm neonates.

5.9 Hypertensive Crisis in Patients with Pheochromocytoma

Hypertensive crisis has occurred after the use of iodinated contrast agents in patient with pheochromocytoma. Monitor patients when administering VISIPAQUE if pheochromocytoma or catecholamine-secreting paragangliomas are suspected. Inject the minimum amount of contrast necessary, assess the blood pressure throughout the procedure, and have measures for treatment of a hypertensive crisis readily available.

5.10 Sickle Cell Crisis in Patients with Sickle Cell Disease

Iodinated contrast agents when administered intravascularly may promote sickling in individuals who are homozygous for sickle cell disease. Hydrate patients prior to and following VISIPAQUE administration and use VISIPAQUE only if the necessary imaging information cannot be obtained with alternative imaging modalities.

5.11 Severe Cutaneous Adverse Reactions

Severe cutaneous adverse reactions (SCAR) may develop from 1 hour to several weeks after intravascular contrast agent administration. These reactions include Stevens-Johnson syndrome and toxic epidermal necrolysis (SJS/TEN), acute generalized exanthematous pustulosis (AGEP) and drug reaction with eosinophilia and systemic symptoms (DRESS). Reaction severity may increase and time to onset may decrease with repeat administration of contrast agents; prophylactic medications may not prevent or mitigate severe cutaneous adverse reactions. Avoid administering VISIPAQUE to patients with a history of a severe cutaneous adverse reaction to VISIPAQUE.

6 ADVERSE REACTIONS

The following clinically significant adverse reactions are described elsewhere in the labeling:

- Risks Associated with Inadvertent Intrathecal Administration [see Warnings and Precautions (5.1)]
- Hypersensitivity Reactions [see Warnings and Precautions (5.2)]
- Contrast-Induced Kidney Injury [see Warnings and Precautions (5.3)]
- Cardiovascular Adverse Reactions [see Warnings and Precautions (5.4)]
- Thromboembolic Events [see Warnings and Precautions (5.5)]
- Thyroid Dysfunction in Pediatric Patients 0 to 3 Years of Age [see Warnings and Precautions (5.8)]
- Severe Cutaneous Adverse Reactions [see Warnings and Precautions (5.11)]

6.1 Clinical Trials Experience

Because clinical trials are conducted under widely varying conditions, adverse reaction rates observed in the clinical trials of a drug cannot be directly compared to rates in the clinical trials of another drug and may not reflect the rates observed in practice.

VISIPAQUE is often associated with sensations of discomfort, warmth or pain. In a subgroup of 1259 patients; 30% who received VISIPAQUE or a comparator had application site discomfort, pain, warmth or cold. VISIPAQUE had a trend toward fewer patient reports of moderate or severe pain or warmth. Pain was reported in 2% of patients receiving VISIPAQUE and 10% of patients receiving a comparator. Heat was reported in 29% of patients receiving VISIPAQUE and 51% of patients receiving a comparator.

Table 3 shows the incidence of events reported in blinded, controlled clinical studies of VISIPAQUE in a total of 1244 adult patients. Adverse events (AEs) are listed by body system and in decreasing order of occurrence greater than 0.5% of patients. One or more adverse events were reported in 20% of patients during the study period (24 to 72 hours). In a 757 patient subgroup, the number of women reporting adverse events was 83/299 (28%) and the number of men was 77/458 (16%). A total of 3% of women and 0.8% of men reported chest pain.

TABLE 3 ADVERSE EVENTS REPORTED IN CONTROLLED CLINICAL TRIALS IN GREATER THAN 0.5% OF 1244 ADULT PATIENTS RECEIVING VISIPAQUE OR OTHER IODINATED CONTRAST AGENTS
NUMBER OF PATIENTS EXPOSED |  | VISIPAQUE N (%) = 1244 | Pooled Comparators N (%) = 861
Number of Patients with Any Adverse Event |  | 248 (19.9) | 194 (22.5)
Body As a Whole | Patients with Any Event | 41 (3.3) | 22 (2.6)
Body As a Whole | Edema (any location) | 7 (0.6) | 0 (0)
Cardiovascular | Patients with Any Event | 37 (3.0) | 39 (4.5)
Cardiovascular | Angina Pectoris/Chest Pain | 28 (2.2) | 22 (2.6)
Gastrointestinal | Patients with Any Event | 51 (4.1) | 46 (5.3)
Gastrointestinal | Diarrhea | 7 (0.6) | 6 (0.7)
Gastrointestinal | Nausea | 35 (2.8) | 32 (3.7)
Gastrointestinal | Vomiting | 10 (0.8) | 11 (1.3)
Nervous System | Patients with Any Event | 101 (8.1) | 60 (7.0)
Nervous System | Agitation, Anxiety, Insomnia, Nervousness | 10 (0.8) | 0 (0)
Nervous System | Dizziness | 8 (0.7) | 8 (0.9)
Nervous System | Headache/Migraine | 31 (2.5) | 15 (1.7)
Nervous System | Paresthesia | 12 (1.0) | 1 (0.1)
Nervous System | Sensory Disturbance | 10 (0.8) | 9 (1.0)
Nervous System | Syncope | 8 (0.6) | 1 (0.1)
Nervous System | Vertigo | 30 (2.4) | 20 (2.3)
Skin (not including application site) | Patients with Any Event | 42 (4.6) | 18 (2.1)
Skin (not including application site) | Nonurticarial Rash or Erythema | 26 (2.1) | 4 (0.5)
Skin (not including application site) | Pruritus | 20 (1.6) | 3 (0.3)
Skin (not including application site) | Urticaria | 6 (0.5) | 10 (1.2)
Special Senses | Patients with Any Event | 57 (4.6) | 38 (4.4)
Special Senses | Parosmia | 6 (0.5) | 4 (0.5)
Special Senses | Taste Perversion | 43 (3.5) | 32 (3.7)
Special Senses | Scotoma | 14 (1.1) | 2 (0.2)

The following selected adverse events were reported in ≤0.5% of the 1244 patients.

Body as a Whole—General Disorders: back pain, fatigue, malaise

Cardiovascular Disorders: arrhythmias, cardiac failure, conduction abnormalities, hypotension, myocardial infarction

Gastrointestinal System Disorders: dyspepsia

Hypersensitivity Disorders: pharyngeal edema

Nervous System: cerebral vascular disorder, convulsions, hypoesthesia, stupor, confusion

Peripheral Vascular Disorders: flushing, peripheral ischemia

Renal System Disorders: abnormal renal function, acute renal failure, hematuria

Respiratory System Disorders: asthma, bronchitis, dyspnea, pulmonary edema, rhinitis

Skin and Appendage Disorders: hematoma, increased sweating

Special Senses, Other Disorders: tinnitus

Vision Disorders: abnormal vision

6.2 Post-marketing Experience

The following additional adverse reactions have been identified during post approval use of VISIPAQUE. Because these reactions are reported voluntarily from a population of uncertain size, it is not always possible to reliably estimate their frequency or establish a causal relationship to exposure.

Cardiovascular Disorders: Cardiac arrest, palpitations, spasms of coronary arteries, hypertension, and flushing

Endocrine Disorders: Hyperthyroidism, hypothyroidism

Eye Disorders: Transient visual impairment including cortical blindness, diplopia, and blurred vision

Gastrointestinal Disorders: Abdominal pain, pancreatitis, salivary gland enlargement

General Disorders and Administration Site Conditions: Chills, pyrexia, pain and discomfort, administration site reactions including extravasation

Immune System Disorders: Hypersensitivity reactions, anaphylactic shock including, life-threatening or fatal anaphylaxis

Nervous System Disorders: Tremor (transient), coma, disturbance in consciousness, transient contrast-induced encephalopathy caused by extravasation of contrast media (including amnesia, hallucination, paralysis, paresis, transient speech disorder, aphasia, dysarthria)

Psychiatric Disorders: Anxiety, agitation

Respiratory, Thoracic, and Mediastinal Disorders: Cough, sneezing, throat irritation or tightness, laryngeal edema, pharyngeal edema, bronchospasm

Skin and subcutaneous tissue disorders: Reactions range from mild (e.g., rash, erythema, pruritus, urticaria, and skin discoloration) to severe: [e.g., Stevens-Johnson syndrome and toxic epidermal necrolysis (SJS/TEN), acute generalized exanthematous pustulosis (AGEP) and drug reaction with eosinophilia and systemic symptoms (DRESS)]

6.3 Pediatric Adverse Reactions

The overall character, quality, and severity of adverse reactions in pediatric patients is similar to that reported in adult patients from post marketing surveillance and other information.

Additional safety data was obtained in studies of VISIPAQUE in 459 pediatric patients. A total of 26 patients ranged in age from birth to <29 days, 148 ranged from 29 days to 2 years, 263 from 2 to <12 years, and 22 from 12 to 18 years. A total of 252 (55%) of the patients were male. The racial distribution was: Caucasian-81%, Black-14%, Oriental-2%, and other or unknown-4%. The proportion of patients undergoing an intra-arterial procedure by age was: 92% (<29 days), 55% (29 days to 6 months), and 29% (>6 months). In these studies, adverse events were numerically higher in pediatric patients less than one year of age compared to older pediatric patients.

In pediatric patients who received intravenous injections of VISIPAQUE for computerized tomography or excretory urography, a concentration of 270 mg Iodine/mL was used in 144 patients, and a concentration of 320 mg Iodine/mL in 154 patients. All patients received one intravenous injection of 1 to 2 mL/kg.

In pediatric patients who received intra-arterial and intracardiac studies, a concentration of 320 mg Iodine/mL was used in 161 patients. Twenty-two patients were < 29 days of age; 78 were 29 days to 2 years of age; and 61 were over 2 years. Most of these pediatric patients received initial volumes of 1 to 2 mL/kg and most patients received a maximum of 3 injections.

7 DRUG INTERACTIONS

7.1 Drug-Drug Interactions

Metformin

In patients with renal impairment, metformin can cause lactic acidosis. Iodinated contrast agents appear to increase the risk of metformin-induced lactic acidosis, possibly as a result of worsening renal function. Stop metformin at the time of, or prior to, VISIPAQUE administration in patients with an eGFR between 30 and 60 mL/min/1.73 m^2; in patients with a history of hepatic impairment, alcoholism or heart failure; or in patients who will be administered intra-arterial iodinated contrast. Re-evaluate eGFR 48 hours after the imaging procedure, and reinstitute metformin only after renal function is stable.

Radioactive Iodine

Administration of iodinated contrast agents may interfere with thyroid uptake of radioactive iodine (I-131 and I-123) and decrease therapeutic and diagnostic efficacy in patients with carcinoma of the thyroid. The decrease in efficacy lasts for 6 to 8 weeks.

Beta-adrenergic Blocking Agents

The use of beta-adrenergic blocking agents lowers the threshold for and increases the severity of contrast reactions, and reduces the responsiveness of treatment of hypersensitivity reactions with epinephrine. Because of the risk of hypersensitivity reactions, use caution when administering VISIPAQUE to patients taking beta-blockers.

Oral Cholecystographic Contrast Agents

Renal toxicity has been reported in patients with liver dysfunction who were given an oral cholecystographic agent followed by intravascular iodinated contrast agents. Postpone the administration of VISIPAQUE in patients who have recently received an oral cholecystographic contrast agent.

7.2 Drug-Laboratory Test Interactions

Effect on Thyroid Tests

The results of protein bound iodine and radioactive iodine uptake studies, which depend on iodine estimation, will not accurately reflect thyroid function for at least 16 days following administration of iodinated contrast agents. However, thyroid function tests which do not depend on iodine estimations (e.g., T3 resin uptake and total or free thyroxine T4 assays) are not affected.

Effect on Urine Tests

As reported with other contrast agents, VISIPAQUE may produce a false-positive result for protein in the urine using urine dip tests. However, the Coomassie blue method has been shown to give accurate results for the measurement of urine protein in the presence of VISIPAQUE. In addition, care should be used in interpreting the results of urine specific gravity measurements in the presence of high levels of VISIPAQUE and other contrast agents in the urine. Refractometry or urine osmolality may be substituted.

8 USE IN SPECIFIC POPULATIONS

8.1 Pregnancy

Risk Summary

There are no data with iodixanol use in pregnant women to inform any drug-associated risks. In animal reproduction studies, no developmental toxicity occurred with intravenous iodixanol administration to rats and rabbits at doses up to 0.24 (rat) or 0.48 (rabbit) times the maximum recommended human intravenous dose (see Data).

All pregnancies have a background risk of birth defect, loss or other adverse outcomes. In the U.S. general population, the estimated background risk of major birth defects and miscarriage in clinically recognized pregnancies is 2 to 4% and 15 to 20%, respectively.

Data

Animal Data

Reproduction studies were performed in rats and rabbits with intravenous administration of iodixanol at doses up to 2 g Iodine/kg, daily, from implantation of the embryo (gestation day 7 in rat; 6 in rabbit) through closure of the hard palate (gestation day 17 in rats; 18 in rabbits). No maternal toxicity occurred, and no adverse effects occurred on fetal survival, embryo-fetal development, or the ability of dams to rear a litter.

8.2 Lactation

Risk Summary

There are no data on the presence of iodixanol in human milk, the effects on the breastfed infant or the effects on milk production. Iodinated contrast agents are poorly excreted into human milk and are poorly absorbed by the gastrointestinal tract of a breastfed infant. The developmental and health benefits of breastfeeding should be considered along with the mother's clinical need for VISIPAQUE and any potential adverse effects on the breastfed infant from VISIPAQUE or from the underlying maternal condition.

Clinical Considerations

Interruption of breastfeeding after exposure to iodinated contrast agents is not necessary because the potential exposure of the breastfed infant to iodine is small. However, a lactating woman may consider interrupting breastfeeding and pumping and discarding breast milk for 10 hours (approximately 5 elimination half-lives) after VISIPAQUE administration in order to minimize drug exposure to a breast fed infant.

8.4 Pediatric Use

The safety and efficacy of VISIPAQUE have been established in pediatric patients down to birth for angiocardiography, cerebral arteriography, visceral arteriography, CT imaging of the head and body, and excretory urography. The safety and efficacy of VISIPAQUE have also been established in pediatric patients 12 years and older for intra-arterial digital subtraction angiography, peripheral arteriography, peripheral venography and CCTA. Use of VISIPAQUE is supported by evidence from adequate and well controlled studies of VISIPAQUE in adults and additional safety data obtained in 459 pediatric patients. In general, the types of adverse reactions reported are similar to those of adults. A higher number of adverse events in patients less than 1 year of age compared to older patients were observed in a study of VISIPAQUE [see Adverse Events (6.3)]. The elimination of VISIPAQUE is slower in this age group [see Clinical Pharmacology (12.3)].

Thyroid function tests indicative of thyroid dysfunction, characterized by hypothyroidism or transient thyroid suppression have been reported following iodinated contrast media administration in pediatric patients, including term and preterm neonates. Some patients were treated for hypothyroidism. After exposure to iodinated contrast media, individualize thyroid function monitoring in pediatric patients 0 to 3 years of age based on underlying risk factors, especially in term and preterm neonates [see Warnings and Precautions (5.8) and Adverse Reactions (6.2)].

Pediatric patients at higher risk of experiencing an adverse reaction during and after administration of any contrast agent may include those with asthma, hypersensitivity to other medication and/or allergens, cyanotic and acyanotic heart disease, congestive heart failure, or a serum creatinine greater than 1.5 mg/dL. Pediatric patients with immature renal function or dehydration may be at increased risk for adverse events due to slower elimination of iodinated contrast agents [see Clinical Pharmacology (12.3)].

8.5 Geriatric Use

In clinical studies of VISIPAQUE, 254/757 (34%) of patients were 65 and over. No overall differences in safety or effectiveness were observed between these patients and younger patients. Other reported clinical experience has not identified differences in response between the elderly and younger patients, but greater sensitivity of some older individuals cannot be ruled out. In general, dose selection for an elderly patient should be cautious usually starting at the low end of the dosing range, reflecting the greater frequency of decreased hepatic, renal or cardiac function, and of concomitant disease or other drug therapy.

10 OVERDOSAGE

The adverse effects of overdosage of any contrast agent may be life-threatening and affect mainly the pulmonary and cardiovascular systems. Treatment of an overdosage is directed toward the support of all vital functions and prompt institution of symptomatic therapy. VISIPAQUE Injection does not bind to plasma or serum protein and can be dialyzed.

11 DESCRIPTION

11.1 Chemical Characteristics

VISIPAQUE (iodixanol) injection is a dimeric, iso-osmolar, nonionic, water-soluble, radiographic contrast medium for intravascular (intravenous and intra-arterial) use. It is provided as a ready-to-use sterile, pyrogen-free, and preservative free, colorless to pale yellow solution.

The chemical formula is 5,5´-[(2-hydroxy-1,3-propanediyl) bis(acetylimino)] bis[N,N´-bis(2,3-dihydroxypropyl)-2,4,6-triiodo-1,3- benzenedicarboxamide] with a molecular weight of 1550.20 (iodine content 49.1%).

VISIPAQUE (C35H44I6N6O15) has the following structural formula:

VISIPAQUE is available in two strengths:

- VISIPAQUE 270 mg Iodine/mL (550 mg Iodixanol/mL), 0.074 mg calcium chloride dihydrate, 1.87 mg sodium chloride, 1.2 mg tromethamine, and 0.1 mg edetate calcium disodium.
- VISIPAQUE 320 mg Iodine/mL (652 mg Iodixanol/mL), 0.044 mg calcium chloride dihydrate, 1.11 mg sodium chloride, 1.2 mg tromethamine and 0.1 mg edetate calcium disodium.

Sodium chloride and calcium chloride have been added, resulting in an isotonic solution for injection providing for both concentrations a sodium/calcium ratio equivalent to blood.

The pH is adjusted to 7.4 with hydrochloric acid and/or sodium hydroxide to achieve a range between pH 6.8 and 7.7 at 22°C.

11.2 Physical Characteristics

The two concentrations of VISIPAQUE Injection (270 mg Iodine/mL and 320 mg Iodine/mL) have the following physical properties:

TABLE 4 Physical Properties of VISIPAQUE
Parameter |  | Concentration (mg Iodine/mL)
 |  | 320 | 270
Osmolality (mOsmol/kg water) |  | 290 | 290
Viscosity (cP) | @ 20°C | 26.6 | 12.7
 | @ 37°C | 11.8 | 6.3
Density (g/mL) | @ 20°C | 1.369 | 1.314
 | @ 37°C | 1.356 | 1.303

12 CLINICAL PHARMACOLOGY

12.1 Mechanism of Action

Intravascular injection of iodixanol opacifies vessels in the path of flow of the contrast agent, permitting visualization of internal structures.

In imaging of the body, iodinated contrast agents diffuse from the vascular into the extravascular space. In a normal brain with an intact blood-brain barrier, contrast does not diffuse into the extravascular space. In patients with a disrupted blood-brain barrier, contrast agent accumulates in the interstitial space in the region of disruption.

12.2 Pharmacodynamics

Following administration of VISIPAQUE, the degree of enhancement is directly related to the iodine content in an administered dose. Peak iodine plasma levels occur immediately following rapid injection. The time to maximum contrast enhancement can vary, depending on the organ, from the time that peak blood iodine concentrations are reached to one hour after intravenous bolus administration. When a delay between peak blood iodine concentrations and peak contrast is present, it suggests that radiographic contrast enhancement is at least in part dependent on the accumulation of iodine- containing medium within the lesion and outside the blood pool.

For angiography, contrast enhancement is greatest immediately (15 seconds to 120 seconds) after rapid injection. Iodinated contrast agents may be visualized in the renal parenchyma within 30 to 60 seconds following rapid intravenous injection. Opacification of the calyces and pelves in patients with normal renal function becomes apparent within 1 to 3 minutes, with optimum contrast occurring within 5 to 15 minutes.

12.3 Pharmacokinetics

Distribution

In an in vitro human plasma study, iodixanol did not bind to protein. The volume of distribution in adults was 0.26 L/kg body weight, consistent with distribution to extracellular space.

Elimination

In 40 healthy, young male volunteers receiving a single intravenous administration of VISIPAQUE in doses of 0.3 to 1.2 gram Iodine/kg body weight, the elimination half-life was 2.1 hr. (± 0.1). Renal clearance was 110 ± 14 mL/min, equivalent to glomerular filtration (108 mL/min). These values were independent of the dose administered.

Metabolism

Iodixanol does not undergo metabolism.

Excretion

In adults, approximately 97% of the injected dose of iodixanol is excreted unchanged in urine within 24 hours, with less than 2% excreted in feces within five days post-injection.

Specific Populations

Pediatric: Forty pediatric patients ≤12 years old, with renal function that is normal for their age, received multiple intra-arterial administrations of VISIPAQUE in doses of 0.32 to 3.2 gram Iodine/kg body weight. The elimination half-lives for these patients are shown in Table 5.

Dose adjustments to account for differences in elimination half-life in pediatric patients less than 6 months of age have not been studied.

TABLE 5 MEAN ELIMINATION HALF-LIFE* IN PEDIATRIC PATIENTS
Age Range | Number of Patients | Elimination half-life
 |  | (hr. ± SD)
Newborn to < 2 months | 8 | 4.1 ± 1.4
2 to 6 months | 8 | 2.8 ± 0.6
6 to 12 months | 9 | 2.4 ± 0.4
1 to 2 years | 5 | 2.3 ± 0.6
2 to 12 years | 10 | 2.3 ± 0.5
Adults | 40 | 2.1 ± 0.1

Renal Impairment: In patients with significantly impaired renal function, the total clearance of iodixanol is reduced and the half-life is increased. In a study of 16 adult patients who were scheduled for renal transplant, the mean creatinine clearance was 13.6 ± 4.7 mL/min). In these patients, plasma half-life was 23 hours (t1/2 for typical patients = 2.1 hours). Contrast enhancement time in kidneys increased from 6 hours to at least 24 hours. Dose adjustments in patients with renal impairment have not been studied. In patients with normal blood brain barriers and severe renal impairment, iodinated contrast agents have been associated with blood-brain barrier disruption and accumulation of contrast in the brain.

VISIPAQUE has been shown to be dialyzable. In an in vitro hemodialysis study, after 4 hours of dialysis with a cellulose membrane, approximately 36% of iodixanol was removed from the plasma. After 4 hours of dialysis with polysulfone membranes, approximately 49% of iodixanol was removed.

13 NONCLINICAL TOXICOLOGY

13.1 Carcinogenesis, Mutagenesis, Impairment of Fertility

Long-term animal studies have not been performed with iodixanol to evaluate carcinogenic potential. Iodixanol was not genotoxic in a series of studies including the Ames test, the CHO/HGPRT assay, a chromosome aberration assay in CHO cells, and a mouse micronucleus assay.

Iodixanol did not impair the fertility of male or female rats when administered at doses up to 0.24 times the maximum recommended human dose.

14 CLINICAL STUDIES

VISIPAQUE was studied in 1244 adult patients. Approximately one-half (590) of the VISIPAQUE patients were 60 years of age or older; the mean age was 56 years (range 18 to 90). A total of patients, 806 (65%) were male. The racial distribution was: Caucasian-85%, Black-12%, Oriental <1%, and other or unknown-3%.

A total of 1235 patients were evaluable for efficacy. Efficacy assessment was based on quality of the radiographic diagnostic visualization (i.e., either: excellent, good, poor, or none) and on the ability to make a diagnosis (i.e., either: confirmed a previous diagnosis, found normal, or diagnosed new findings).

14.1 Intra-arterial Administration Studies

Angiocardiography, cerebral arteriography, peripheral arteriography, and visceral arteriography were studied with either one or both concentrations of VISIPAQUE Injection (270 mg Iodine/mL or 320 mg Iodine/mL). In these intra-arterial studies, diagnostic visualization ratings were good or excellent in all the patients and a radiologic diagnosis was made in all of the patients. In additional intra-arterial studies, overall quality of diagnostic visualization was rated optimal in the majority of patients and a radiologic diagnosis was made in all (100%) of the patients. The number of patients studied in each indication is provided below.

Angiocardiography was evaluated in two randomized, double-blind clinical studies in 101 adult patients given VISIPAQUE 320 mg Iodine/mL. Seven additional angiocardiography studies were performed in 217 adult patients given VISIPAQUE 320 mg Iodine/mL. Visualization ratings were good or excellent in all the patients given VISIPAQUE; a radiologic diagnosis was made in the majority of the patients. Confirmation of the radiologic findings by other diagnostic methods was not obtained.

Cerebral arteriography was evaluated in two randomized, double-blind clinical trials in 51 adult patients given VISIPAQUE 320 mg Iodine/mL. Two additional cerebral arteriography studies were performed in 15 adult patients given VISIPAQUE Injection 270 mg Iodine/mL, 40 patients given VISIPAQUE 320 mg Iodine/mL. Visualization ratings were good or excellent in all the patients a radiologic diagnosis was made in the majority of the patients. Confirmation of the radiologic findings by other diagnostic methods was not obtained.

Peripheral arteriography was evaluated in two randomized, double-blind clinical trials in 49 adult patients given VISIPAQUE 320 mg Iodine/mL. Four additional peripheral arteriography studies were performed in 41 adult patients given VISIPAQUE 270 mg Iodine/mL, 85 patients given VISIPAQUE 320 mg Iodine/mL. Visualization ratings were good or excellent in 100% of the patients given VISIPAQUE; a radiologic diagnosis was made in the majority of the patients. Confirmation of the radiologic findings by other diagnostic methods was not obtained.

Visceral arteriography was evaluated in two randomized, double-blind clinical trials in 55 adult patients given VISIPAQUE 320 mg Iodine/mL. Visualization ratings were good or excellent in all of the patients; a radiologic diagnosis was made in the majority of the patients. Confirmation of the radiologic findings by other diagnostic methods was not obtained.

Similar studies with digital subtraction angiography (DSA) were completed with comparable findings noted in cerebral arteriography, peripheral arteriography, and visceral arteriography. Studies have not been conducted to determine the lowest effective concentration of VISIPAQUE.

14.2 Intravenous Administration Studies

Excretory urography, computed tomography (CT) of the head, CT of the body, peripheral venography, and coronary computed tomography angiography (CCTA) were studied with either one or both VISIPAQUE Injection concentrations (270 mg Iodine/mL or 320 mg Iodine/mL). In the non-CCTA intravenous studies, diagnostic visualization ratings were good or excellent in 96-100% of the patients and a radiologic diagnosis was made in all of the patients given VISIPAQUE. In the CCTA studies results were computed in terms of sensitivity and specificity compared to a standard of reference. The number of patients studied in each indication is provided below.

Excretory urography was evaluated in one uncontrolled, unblinded clinical trial in 40 patients, 20 given VISIPAQUE 270 mg Iodine/mL and 20 given VISIPAQUE 320 mg Iodine/mL, and in two randomized, double-blind clinical trials in 50 adult patients given VISIPAQUE 270 mg Iodine/mL, 50 patients given VISIPAQUE 320 mg Iodine/mL. Visualization ratings were good or excellent in all of the patients given VISIPAQUE; a radiologic diagnosis was made in the majority of the patients. Confirmation of the radiologic findings by other diagnostic methods was not obtained.

CT of the head was evaluated in two randomized, double-blind clinical trials in 49 adult patients given VISIPAQUE 270 mg Iodine/mL, in 50 patients given VISIPAQUE 320 mg Iodine/mL. CT of the body was evaluated in three randomized, double-blind clinical trials in 104 adult patients given VISIPAQUE 270 mg Iodine/mL, and 109 patients given VISIPAQUE 320 mg Iodine/mL. In both CT of the head and body, visualization ratings were good or excellent in all of the patients given VISIPAQUE; a radiologic diagnosis was made in the majority of the patients. Confirmation of the radiologic findings by other diagnostic methods was not obtained.

Peripheral venography was evaluated in two randomized, double-blind clinical studies in 46 adult patients given VISIPAQUE 270 mg Iodine/mL. Visualization ratings were good or excellent in all of the patients given VISIPAQUE; a radiologic diagnosis was made in the majority of the patients. The results were similar to those of the active control. Confirmation of the radiologic findings by other diagnostic methods was not obtained.

VISIPAQUE 320 mg Iodine/mL for CCTA was evaluated in two prospective, multicenter clinical studies in a total of 1106 adult patients. The patient population consisted of stable outpatients with chest pain or other symptoms suggestive of coronary artery disease, and no known history of coronary disease. All the CCTAs were done using 64 detector row CT scanners. Most of the patients received beta-blocker medication for heart rate control and nitroglycerin for vasodilation. Patients with irregular cardiac rhythm or heart rate above 100 beats per minute were excluded. The mean patient age was 57 years in the first study and 59 years in the second study. Both studies had more men than women (59% male in the first study and 51% male in the second study), and more Caucasian patients (88% in the first study and 78% in the second study) than Black, Asian, or other patients. The BMI range was 17 to 50 with a mean of 31 in the first study and a BMI range of 15 to 71 with a mean of 30 in the second study.

In the first study, 230 patients (906 vessels) were evaluable for efficacy using the reference standard of invasive coronary angiography. Seventy-five vessels (8%, in 49 patients) were evaluated as positive for ≥ 50% stenosis. The CCTA images were randomized and read by three blinded, independent readers; the coronary angiography images were interpreted by an independent, blinded reader. Assuming independence between vessels, the vessel-level sensitivity (95% CI) for assessing ≥ 50% stenosis was 76% (63, 86) for reader 1, 89% (79, 95) for reader 2 and 77% (65, 86) for reader 3. The vessel-level specificity (95% CI) was 85% (81, 89) for reader 1, 84% (81, 87) for reader 2, and 89% (86, 91) for reader 3. The vessel-level sensitivity and specificity for assessing ≥ 70% stenosis were similar.

In a second study, 857 patients were evaluable for efficacy. Patients were followed up for 12 months after CCTA and the reference standard was a composite of pre-specified clinical outcomes (death, major adverse cardiac event, or coronary revascularization). Seventy-six patients (9%) experienced one or more of the pre-specified outcomes over 12 months of follow-up. The sensitivity (95% CI) and specificity (95% CI) of a positive CCTA finding (≥ 50% stenosis at the patient level) to predict one or more of the pre-specified clinical outcomes was 95% (87, 99) and 87% (84, 89), respectively.

16 HOW SUPPLIED/STORAGE AND HANDLING

16.1 How Supplied

VISIPAQUE injection is a ready-to-use sterile, pyrogen-free, preservative free, colorless to pale yellow solution available in two (2) strengths. It is supplied in the following configurations:

VISIPAQUE (iodixanol) Injection 270 mg Iodine/mL:

50 mL in single-dose +PLUSPAK™ (polymer bottle), boxes of 10 | (NDC 0407-2222-16)
100 mL in single-dose +PLUSPAK™ (polymer bottle), boxes of 10 | (NDC 0407-2222-17)
150 mL in single-dose +PLUSPAK™ (polymer bottle), boxes of 10 | (NDC 0407-2222-19)
200 mL in single-dose +PLUSPAK™ (polymer bottle), boxes of 10 | (NDC 0407-2222-21)

VISIPAQUE (iodixanol) Injection 320 mg Iodine/mL:

50 mL in single-dose +PLUSPAK™ (polymer bottle), boxes of 10 | (NDC 0407-2223-16)
100 mL in single-dose +PLUSPAK™ (polymer bottle), boxes of 10 | (NDC 0407-2223-17)
150 mL in single-dose +PLUSPAK™ (polymer bottle), boxes of 10 | (NDC 0407-2223-19)
200 mL in single-dose +PLUSPAK™ (polymer bottle), boxes of 10 | (NDC 0407-2223-21)

16.2 Storage and Handling

Protect VISIPAQUE from direct exposure to sunlight.

Store VISIPAQUE at controlled room temperature, 20°C to 25°C (68°F to 77°F); excursions permitted to 15°C to 30°C (59°F to 86°F) [see USP Controlled Room Temperature].

VISIPAQUE may be stored in a contrast media warmer for up to one month at 37°C (98.6°F).

Do not freeze. Discard any product that is inadvertently frozen, as freezing may compromise the closure integrity of the immediate container.

17 PATIENT COUNSELING INFORMATION

Hypersensitivity Reactions

Advise the patient concerning the risk of hypersensitivity reactions that can occur both during and after VISIPAQUE administration. Advise the patient to report any signs or symptoms of hypersensitivity reactions during the procedure and to seek immediate medical attention for any signs or symptoms experienced after discharge [see Warnings and Precautions (5.2)].

Advise patients to inform their physician if they develop a rash after receiving VISIPAQUE [see Warnings and Precautions (5.11)].

Contrast-Induced Acute Kidney Injury

Advise the patient concerning appropriate hydration to decrease the risk of contrast-induced acute kidney injury [see Warnings and Precautions (5.3)].

Extravasation

If extravasation occurs during injection, advise patients to seek medical care for progression of symptoms [see Warnings and Precautions (5.6)].

Thyroid Dysfunction

Advise parents/caregivers about the risk of developing thyroid dysfunction after VISIPAQUE administration. Advise parents/caregivers about when to seek medical care for their child to monitor for thyroid dysfunction [see Warnings and Precautions (5.8)].

Distributed by GE Healthcare Inc., Arlington Heights, IL 60004 U.S.A.

Product of Norwegian Origin.

VISIPAQUE is a trademark of GE HealthCare or one of its subsidiaries.

GE is a trademark of General Electric Company used under trademark license.

© 2025 GE HealthCare

GE Healthcare

V-552

Contains
10 x 100 mL
Bottles

PRINCIPAL DISPLAY PANEL - 100 mL Bottle Box Label - 2222

V-552

Contains
10 x 100 mL
Bottles

NDC 0407-2222-17

VISIPAQUE™
(iodixanol) Injection

270 mgI/mL

NOT FOR INTRATHECAL USE

in +PLUSPAK™ (polymer bottle)

Single-Dose Bottle
Sterile Aqueous Injection

Each 1 mL contains 550 mg of iodixanol (270 mg organically bound iodine), 0.074 mg calcium
chloride dihydrate, 1.87 mg sodium chloride, 1.2 mg tromethamine, and 0.1 mg edetate
calcium disodium. The pH is adjusted to 7.4 with hydrochloric acid and/or sodium hydroxide
to achieve a range between pH 6.8-7.7. Osmolality is 290 mOsm/kg water.
No preservative added. Each unit for one procedure only.
Discard unused portion. Protect from light if removed
from carton. Store at 20°-25°C (68°-77°F); excursions
permitted to 15°-30°C (59°-86°F) [see USP].
Do not freeze. For indications and dosage,
see prescribing information.
RX ONLY

Distributed by GE Healthcare Inc.,
Arlington Heights, IL 60004 U.S.A.
For inquiries call 1-800-654-0118

Product of Norwegian Origin.

(01)20304072222174

Exp.:
Lot:

1209190 USA GE HealthCare

PRINCIPAL DISPLAY PANEL - 100 mL Bottle Box Label - 2223

V-562

Contains
10 x 100 mL
Bottles

NDC 0407-2223-17

VISIPAQUE™
(iodixanol) Injection

320 mg Iodine/mL

For Intra-arterial and
Intravenous Use Only

in +PLUSPAK™ (polymer bottle)

Single-Dose Bottle
Sterile Aqueous Solution

NOT FOR INTRATHECAL USE

For CT of the head and body,
VISIPAQUE™ may be used with an
automated contrast injection system
or contrast media management system
cleared for use with VISIPAQUE™.

Each 1 mL contains 652 mg of iodixanol (320 mg organically bound iodine), 0.044 mg calcium
chloride dihydrate, 1.11 mg sodium chloride, 1.2 mg tromethamine, and 0.1 mg edetate
calcium disodium. The pH is adjusted to 7.4 with hydrochloric acid and/or sodium hydroxide
to achieve a range between pH 6.8-7.7. Osmolality is 290 mOsm/kg water.
No preservative added. Each unit for one procedure only.
If used with an automated contrast management system,
maximum use time is 4 hours after initial puncture.
Discard unused portion. Protect from light if removed
from carton. Store at 20°-25°C (68°-77°F); excursions
permitted to 15°-30°C (59°-86°F) [see USP].
Do not freeze. For indications and dosage,
see prescribing information.
RX ONLY

Distributed by GE Healthcare Inc.,
Arlington Heights, IL 60004 U.S.A.
For inquiries call 1-800-654-0118

Product of Norwegian Origin.

(01)20304072223171

Exp.:
Lot:

1209198 USA GE HealthCare